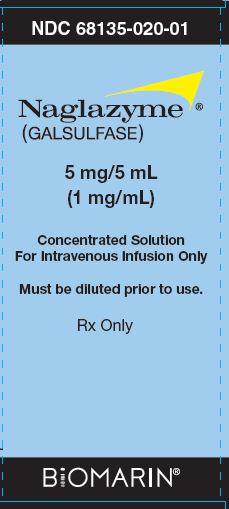 DRUG LABEL: NAGLAZYME
NDC: 68135-020 | Form: SOLUTION
Manufacturer: BioMarin Pharmaceutical Inc.
Category: prescription | Type: HUMAN PRESCRIPTION DRUG LABEL
Date: 20240918

ACTIVE INGREDIENTS: GALSULFASE 5 mg/5 mL

HIGHLIGHTS OF PRESCRIBING INFORMATION

These highlights do not include all the information needed to use NAGLAZYME® safely and effectively. See full prescribing information for NAGLAZYME.
NAGLAZYME (galsulfase) injection, for intravenous use
Initial U.S. Approval: 2005

WARNING: HYPERSENSITIVITY REACTIONS INCLUDING ANAPHYLAXIS

See full prescribing information for complete boxed warning.

- Anaphylaxis has occurred during the early course of enzyme replacement therapy and after extended duration of therapy. (5.1)
- Initiate NAGLAZYME in a healthcare setting with appropriate medical monitoring and support measures, including access to cardiopulmonary resuscitation equipment. (5.1)
- If a severe hypersensitivity reaction (e.g., anaphylaxis) occurs, discontinue NAGLAZYME and immediately initiate appropriate medical treatment, including use of epinephrine. (5.1)

RECENT MAJOR CHANGES

Boxed Warning | 7/2024
Dosage and Administration (2.1) | 7/2024
Warnings and Precautions (5.1) | 7/2024

1 INDICATIONS AND USAGE

NAGLAZYME is a hydrolytic lysosomal glycosaminoglycan (GAG)-specific enzyme indicated for patients with Mucopolysaccharidosis VI (MPS VI; Maroteaux-Lamy syndrome). NAGLAZYME has been shown to improve walking and stair-climbing capacity. (1)

2 DOSAGE AND ADMINISTRATION

Administration of NAGLAZYME should be supervised by a healthcare provider knowledgeable in the management of hypersensitivity reactions including anaphylaxis. (2.1)

The recommended dosage is 1 mg per kg of body weight administered once weekly as an intravenous infusion. (2.2)

3 DOSAGE FORMS AND STRENGTHS

Injection: 5 mg/5 mL (1 mg/mL) in a single-dose vial. (3)

4 CONTRAINDICATIONS

None. (4)

5 WARNINGS AND PRECAUTIONS

- Immune-Mediated Reactions: Immune-mediated reactions can occur with NAGLAZYME. Monitor patients for the development of immune complex-mediated reactions while receiving NAGLAZYME. (5.2)
- Risk of Acute Cardiorespiratory Failure: Caution should be exercised when administering NAGLAZYME to patients susceptible to fluid volume overload. Consider a decreased total infusion volume and infusion rate when administering NAGLAZYME to these patients. Appropriate medical monitoring and support measures should be available during infusion. (2.2, 5.3)
- Acute Respiratory Complications: Sleep apnea is common in MPS VI patients and antihistamine pretreatment may increase the risk of apneic episodes. Appropriate respiratory support should be available during infusion. (5.4)
- Infusion Reactions: Pretreatment with antihistamines with or without antipyretics is recommended prior to the start of infusion to reduce the risk of infusion-reactions. If infusion reactions occur, decreasing the infusion rate, temporarily stopping the infusion, or administering additional antihistamines and/or antipyretics is recommended. (2.2, 5.5)

6 ADVERSE REACTIONS

The most common adverse reactions (≥10%) are: rash, pain, urticaria, pyrexia, pruritus, chills, headache, nausea, vomiting, abdominal pain and dyspnea. The most common adverse reactions requiring interventions are infusion-related reactions. (6.1)

To report SUSPECTED ADVERSE REACTIONS, contact: BioMarin Pharmaceutical Inc. at 1-866-906-6100 or FDA at 1-800-FDA-1088 or www.fda.gov/medwatch.

FULL PRESCRIBING INFORMATION

WARNING: HYPERSENSITIVITY REACTIONS INCLUDING ANAPHYLAXIS

Patients treated with enzyme replacement therapies have experienced life-threatening hypersensitivity reactions, including anaphylaxis. Anaphylaxis has occurred during the early course of enzyme replacement therapy and after extended duration of therapy.

Initiate NAGLAZYME in a healthcare setting with appropriate medical monitoring and support measures, including access to cardiopulmonary resuscitation equipment. If a severe hypersensitivity reaction (e.g., anaphylaxis) occurs, discontinue NAGLAZYME and immediately initiate appropriate medical treatment, including use of epinephrine.

Inform patients of the symptoms of life-threatening hypersensitivity reactions, including anaphylaxis and to seek immediate medical care should symptoms occur [see Warnings and Precautions (5.1)].

1 INDICATIONS AND USAGE

NAGLAZYME is indicated for patients with Mucopolysaccharidosis VI (MPS VI, Maroteaux-Lamy syndrome). NAGLAZYME has been shown to improve walking and stair-climbing capacity.

2 DOSAGE AND ADMINISTRATION

2.1 Recommendations Prior to NAGLAZYME Treatment

Administration of NAGLAZYME should be supervised by a healthcare provider knowledgeable in the management of hypersensitivity reactions including anaphylaxis [see Warnings and Precautions (5.1)].

Initiate NAGLAZYME in a healthcare setting with appropriate medical monitoring and support measures, including access to cardiopulmonary resuscitation equipment [see Warnings and Precautions (5.1)].

Pretreatment with antihistamines with or without antipyretics is recommended 30 to 60 minutes prior to the start of the infusion [see Warnings and Precautions (5.5)].

2.2 Recommended Dosage and Administration

The recommended dosage regimen of NAGLAZYME is 1 mg per kg of body weight administered once weekly as an intravenous infusion.

The total volume of the infusion should be delivered over a period of time of no less than 4 hours. NAGLAZYME should be diluted with 0.9% Sodium Chloride Injection, USP, to a final volume of 250 mL and delivered by controlled intravenous infusion using an infusion pump. The initial infusion rate should be 6 mL per hour for the first hour. If the infusion is well tolerated, the rate of infusion may be increased to 80 mL per hour for the remaining 3 hours. The infusion time can be extended up to 20 hours if infusion reactions occur.

For patients 20 kg and under or those who are susceptible to fluid volume overload, physicians may consider diluting NAGLAZYME in a volume of 100 mL [see Warnings and Precautions (5.3)]. The infusion rate (mL per hour) should be decreased so that the total infusion duration remains no less than 4 hours.

Each vial of NAGLAZYME provides 5 mg of galsulfase (expressed as protein content) in 5 mL of solution and is intended for single use only. Do not use the vial more than one time. The concentrated solution for infusion must be diluted with 0.9% Sodium Chloride Injection, USP, using aseptic techniques. Prepare NAGLAZYME using low-protein-binding containers and administer the diluted NAGLAZYME solution to patients using a low-protein-binding infusion set equipped with a low-protein-binding 0.2 µm in-line filter. There is no information on the compatibility of diluted NAGLAZYME with glass containers.

2.3 Instructions for Use

Prepare and use NAGLAZYME according to the following steps. Use aseptic techniques.

1. Determine the number of vials to be used based on the patient's weight and the recommended dose of 1 mg per kg:
  Patient's weight (kg) × 1 mL/kg of NAGLAZYME = Total number of mL of NAGLAZYME
  Total number of mL of NAGLAZYME ÷ 5 mL per vial = Total number of vials
  Round up to the next whole vial. Remove the required number of vials from the refrigerator to allow them to reach room temperature. Do not allow vials to remain at room temperature longer than 24 hours prior to dilution. Do not heat or microwave vials.
2. Before withdrawing the NAGLAZYME solution from the vial, visually inspect each vial for particulate matter and discoloration. The NAGLAZYME solution should be clear to slightly opalescent and colorless to pale yellow. Some translucency may be present in the solution. Do not use if the solution is discolored or if there is particulate matter in the solution.
3. From a 250 mL infusion bag of 0.9% Sodium Chloride Injection, USP, withdraw and discard a volume equal to the volume of NAGLAZYME solution to be added. If using a 100 mL infusion bag, this step is not necessary.
4. Slowly withdraw the calculated volume of NAGLAZYME from the appropriate number of vials using caution to avoid excessive agitation. Do not use a filter needle, as this may cause agitation. Agitation may denature NAGLAZYME, rendering it biologically inactive.
5. Slowly add the NAGLAZYME solution to the 0.9% Sodium Chloride Injection, USP, using care to avoid agitation of the solutions. Do not use a filter needle.
6. Gently rotate the infusion bag to ensure proper distribution of NAGLAZYME. Do not shake the solution.
7. Administer the diluted NAGLAZYME solution to patients using a low-protein-binding infusion set equipped with a low-protein-binding 0.2 µm in-line filter.

NAGLAZYME does not contain preservatives; therefore, after dilution with saline, the infusion bags should be used immediately. If immediate use is not possible, the diluted solution must be stored refrigerated at 2°C to 8°C (36°F to 46°F) and administered within 48 hours from the time of dilution to completion of administration. Other than during infusion, do not store the diluted NAGLAZYME solution at room temperature. Any unused product or waste material must be discarded and disposed of in accordance with local requirements.

NAGLAZYME must not be infused with other products in the infusion tubing. The compatibility of NAGLAZYME in solution with other products has not been evaluated.

3 DOSAGE FORMS AND STRENGTHS

Injection: 5 mg/5 mL (1 mg/mL) as a colorless to pale yellow, clear to slightly opalescent solution single-dose vials

4 CONTRAINDICATIONS

None.

5 WARNINGS AND PRECAUTIONS

5.1 Hypersensitivity Reactions Including Anaphylaxis

Life-threatening hypersensitivity reactions, including anaphylaxis, have been observed in patients treated with enzyme replacement therapies, including NAGLAZYME. These reactions have occurred during and up to 24 hours after completion of the NAGLAZYME infusion. Some of the reactions included shock, respiratory distress, dyspnea, bronchospasm, laryngeal edema, and hypotension [see Adverse Reactions (6.1, 6.2)].

Anaphylaxis has occurred during the early course of enzyme replacement therapy and after extended duration of therapy. Administration of NAGLAZYME should be supervised by a healthcare provider knowledgeable in the management of hypersensitivity reactions including anaphylaxis. Initiate NAGLAZYME in a healthcare setting with appropriate medical monitoring and support measures, including access to cardiopulmonary resuscitation equipment.

If a severe hypersensitivity reaction (e.g., anaphylaxis) occurs, discontinue NAGLAZYME and immediately initiate appropriate medical treatment, including use of epinephrine. In patients who have experienced anaphylaxis or other serious hypersensitivity reactions during infusion with NAGLAZYME, caution should be exercised upon rechallenge.

Inform patients of the symptoms of life-threatening hypersensitivity reactions, including anaphylaxis and to seek immediate medical care should symptoms occur.

5.2 Immune-Mediated Reactions

Type III immune complex-mediated reactions, including membranous glomerulonephritis have been observed with NAGLAZYME, as with other enzyme replacement therapies. If immune-mediated reactions occur, discontinuation of the administration of NAGLAZYME should be considered, and appropriate medical treatment initiated. The risks and benefits of re-administering NAGLAZYME following an immune-mediated reaction should be considered. Some patients have successfully been rechallenged and have continued to receive NAGLAZYME under close clinical supervision [see Adverse Reactions (6.2)].

5.3 Risk of Acute Cardiorespiratory Failure

Caution should be exercised when administering NAGLAZYME to patients susceptible to fluid volume overload, such as patients weighing 20 kg or less, patients with acute underlying respiratory illness, or patients with compromised cardiac and/or respiratory function, because congestive heart failure may result. Appropriate medical support and monitoring measures should be readily available during NAGLAZYME infusion and some patients may require prolonged observation times that should be based on the individual needs of the patient [see Adverse Reactions (6.2)].

5.4 Acute Respiratory Complications Associated with Administration

Sleep apnea is common in MPS VI patients and antihistamine pretreatment may increase the risk of apneic episodes. Evaluation of airway patency should be considered prior to initiation of treatment. Patients using supplemental oxygen or continuous positive airway pressure (CPAP) during sleep should have these treatments readily available during infusion in the event of an infusion reaction, or extreme drowsiness/sleep induced by antihistamine use.

Consider delaying NAGLAZYME infusions in patients who present with an acute febrile or respiratory illness because of the possibility of acute respiratory compromise during infusion of NAGLAZYME.

5.5 Infusion Reactions

Because of the potential for infusion reactions, patients should receive antihistamines with or without antipyretics prior to infusion. Despite routine pretreatment with antihistamines, infusion reactions, some severe, occurred in 33 of 59 (56%) patients treated with NAGLAZYME. Serious adverse reactions during infusion included laryngeal edema, apnea, pyrexia, urticaria, respiratory distress, angioedema, and anaphylactoid reaction. Severe adverse reactions included urticaria, chest pain, rash, dyspnea, apnea, laryngeal edema, and conjunctivitis [see Adverse Reactions (6.1, 6.2)].

The most common symptoms of drug-related infusion reactions were pyrexia, chills, rash, urticaria, dyspnea, nausea, vomiting, pruritis, erythema, abdominal pain, hypertension, and headache. Respiratory distress, chest pain, hypotension, angioedema, conjunctivitis, tremor, and cough were also reported. Infusion reactions began as early as Week 1 and as late as Week 146 of NAGLAZYME treatment. Twenty-three of 33 patients (70%) experienced recurrent infusion reactions during multiple infusions though not always in consecutive weeks.

Symptoms typically abated with slowing or temporary interruption of the infusion and administration of additional antihistamines, antipyretics, and occasionally corticosteroids. Most patients were able to complete their infusions. Subsequent infusions were managed with a slower rate of NAGLAZYME administration, treatment with additional prophylactic antihistamines, and, in the event of a more severe reaction, treatment with prophylactic corticosteroids.

If severe infusion reactions occur, immediately discontinue the infusion of NAGLAZYME and initiate appropriate treatment. The risks and benefits of re-administering NAGLAZYME following a severe reaction should be considered.

No factors were identified that predisposed patients to infusion reactions. There was no association between severity of infusion reactions and titer of anti-galsulfase antibodies.

5.6 Spinal or Cervical Cord Compression

Spinal or cervical cord compression (SCC) with resultant myelopathy is a known and serious complication of MPS VI. SCC is expected to occur in the natural history of the disease, including in patients on NAGLAZYME. There have been postmarketing reports of patients treated with NAGLAZYME who experienced the onset or worsening of SCC requiring decompression surgery. Patients with MPS VI should be monitored for signs and symptoms of spinal/cervical cord compression (including back pain, paralysis of limbs below the level of compression, urinary and fecal incontinence) and given appropriate clinical care.

6 ADVERSE REACTIONS

Serious and/or clinically significant adverse reactions described elsewhere in labeling include:

- Hypersensitivity Reactions Including Anaphylaxis [see Warnings and Precautions (5.1)]
- Immune-Mediated Reactions [see Warnings and Precautions (5.2)]
- Risk of Acute Cardiorespiratory Failure [see Warnings and Precautions (5.2)]
- Acute Respiratory Complications Associated with Administration [see Warnings and Precautions (5.4)]
- Infusion Reactions [see Warnings and Precautions (5.5)]
- Spinal or Cervical Cord Compression [see Warnings and Precautions (5.6)]

6.1 Clinical Trials Experience

Because clinical trials are conducted under widely varying conditions, adverse reaction rates observed in the clinical trials of a drug cannot be directly compared to rates observed in the clinical trials of another drug and may not reflect the rates observed in clinical practice.

NAGLAZYME was studied in a randomized, double-blind, placebo-controlled trial in which 19 patients received weekly infusions of 1 mg/kg NAGLAZYME and 20 patients received placebo; of the 39 patients 66% were female, and 62% were White, non-Hispanic. Patients were aged 5 years to 29 years. NAGLAZYME-treated patients were approximately 3 years older than placebo-treated patients (mean age 13.7 years versus 10.7 years, respectively).

Serious adverse reactions experienced in this trial include apnea, pyrexia, and respiratory distress. Severe adverse reactions include chest pain, dyspnea, laryngeal edema, and conjunctivitis. The most common adverse reactions requiring interventions were infusion reactions.

Table 1 summarizes the adverse reactions that occurred in the placebo-controlled trial in at least 2 patients more in the NAGLAZYME‑treated group than in the placebo-treated group.

Table 1: Adverse Reactions that Occurred in the Placebo-Controlled Trial in at least 2 Patients More in the NAGLAZYME Group than in the Placebo Group
 | NAGLAZYME (n = 19) | Placebo (n = 20 [One of the 20 patients in the placebo group dropped out after Week 4 infusion])
MedDRA Preferred Term | No. Patients (%) | No. Patients (%)
All | 19 (100) | 20 (100)
Abdominal Pain | 9 (47) | 7 (35)
Ear Pain | 8 (42) | 4 (20)
Arthralgia | 8 (42) | 5 (25)
Pain | 6 (32) | 1 (5)
Conjunctivitis | 4 (21) | 0
Dyspnea | 4 (21) | 2 (10)
Rash | 4 (21) | 2 (10)
Chills | 4 (21) | 0
Chest Pain | 3 (16) | 1 (5)
Pharyngitis | 2 (11) | 0
Areflexia | 2 (11) | 0
Corneal Opacity | 2 (11) | 0
Gastroenteritis | 2 (11) | 0
Hypertension | 2 (11) | 0
Malaise | 2 (11) | 0
Nasal Congestion | 2 (11) | 0
Umbilical Hernia | 2 (11) | 0
Hearing Impairment | 2 (11) | 0

Four open-label clinical trials were conducted in MPS VI patients aged 3 months to 29 years with NAGLAZYME administered at doses of 0.2 mg/kg (n = 2), 1 mg/kg (n = 55), and 2 mg/kg (n = 2). The mean exposure to the recommended dose of NAGLAZYME (1 mg/kg) was 138 weeks (range = 54 to 261 weeks). Two infants (12.1 months and 12.7 months) were exposed to 2 mg/kg of NAGLAZYME for 105 and 81 weeks, respectively.

In addition to those listed in Table 1, common adverse reactions observed in the open-label trials include pruritus, urticaria, pyrexia, headache, nausea, and vomiting. The most common adverse reactions requiring interventions were infusion reactions. Serious adverse reactions included laryngeal edema, urticaria, angioedema, and other hypersensitivity reactions. Severe adverse reactions included urticaria, rash, and abdominal pain.

Observed adverse events in four open-label studies (up to 261 weeks treatment) were not different in nature or severity to those observed in the placebo-controlled study. No patients discontinued during open-label treatment with NAGLAZYME due to adverse events.

6.2 Postmarketing Experience

The following adverse reactions have been identified during post approval use of NAGLAZYME. Because these reactions are reported voluntarily from a population of uncertain size, it is not always possible to reliably estimate their frequency or establish a causal relationship to drug exposure.

Serious infusion reactions: anaphylaxis, shock, hypotension, bronchospasm, and respiratory failure [see Warnings and Precautions (5.1)].

Additional infusion reactions: pyrexia, erythema, pallor, bradycardia, tachycardia, hypoxia, cyanosis, tachypnea, and paresthesia.

During postmarketing surveillance, there has been a single case of membranous nephropathy and rare cases of thrombocytopenia reported. In the case of membranous nephropathy, renal biopsy revealed galsulfase‑immunoglobulin complexes in the glomeruli. With both membranous nephropathy and thrombocytopenia, patients have been successfully rechallenged and have continued to receive NAGLAZYME.

8 USE IN SPECIFIC POPULATIONS

8.1 Pregnancy

Risk Summary

Available data from a pregnancy sub-study within the MPS VI Clinical Surveillance Program and case reports with NAGLAZYME use in pregnant women have not identified a drug-associated risk of major birth defects, miscarriage, or adverse maternal or fetal outcomes. In animal reproduction studies, galsulfase administered intravenously to pregnant rats and rabbits during the period of organogenesis, showed no evidence of harm to the fetus at doses of about 0.5 and 0.97 times, respectively for rats and rabbits, the recommended human dose of 1 mg/kg based on body surface area (see Data).

The estimated background risk of major birth defects and miscarriage for the indicated population is unknown. All pregnancies have a background risk of birth defects, loss, or other adverse outcomes. In the U.S. general population, the estimated background risk of major birth defects and miscarriage in clinically recognized pregnancies is 2% to 4% and 15% to 20%, respectively.

Clinical Considerations

Disease-associated maternal and embryo/fetal risk

Pregnancy can exacerbate preexisting clinical manifestations of MPS and lead to adverse pregnancy outcomes for both mother and fetus.

Data

Human Data

Available data from a pregnancy sub-study within the MPS VI Clinical Surveillance Program and case reports with the use of NAGLAZYME during pregnancy have identified seventeen pregnancies. No major birth defects have been reported. Drug-associated adverse maternal and fetal outcomes have not been identified.

Animal Data

Reproduction studies have been performed with intravenous galsulfase during the period of organogenesis in pregnant rats at doses of galsulfase up to 3 mg/kg/day (about 0.5 times the recommended human dose of 1 mg/kg based on the body surface area) and in pregnant rabbits at doses up to 3 mg/kg/day (about 0.97 times the recommended human dose of 1 mg/kg based on the body surface area) and have revealed no evidence of harm to the fetus due to galsulfase.

8.2 Lactation

Risk Summary

There are no data on the presence of galsulfase in human milk, the effects on the breastfed infant, or the effects on milk production. The developmental and health benefits of breastfeeding should be considered along with the mother’s clinical need for NAGLAZYME and any potential adverse effects on the breastfed infant from NAGLAZYME or from the underlying maternal condition.

8.4 Pediatric Use

Clinical studies with NAGLAZYME were conducted in 56 patients, ages 5 to 29 years, with the majority of these patients in the pediatric age group [see Clinical Studies (14)]. In addition, an open-label study was conducted in four infants (3 months to 12.7 months) treated with 1 mg/kg (n = 2) or 2 mg/kg (n = 2) of NAGLAZYME. Safety results in infants were consistent with results observed in patients 5 to 29 years old [see Adverse Reactions (6)].

8.5 Geriatric Use

Clinical studies of NAGLAZYME did not include patients older than 29 years of age. It is not known whether older patients respond differently from younger patients.

11 DESCRIPTION

NAGLAZYME is a formulation of galsulfase, which is a purified human enzyme that is produced by recombinant DNA technology in a Chinese hamster ovary cell line. Galsulfase (glycosaminoglycan N-acetylgalactosamine 4-sulfatase, EC 3.1.6.12) is a lysosomal enzyme that catalyzes the cleavage of the sulfate ester from terminal N–acetylgalactosamine 4-sulfate residues of glycosaminoglycans (GAG), chondroitin 4-sulfate and dermatan sulfate.

Galsulfase is a glycoprotein with a molecular weight of approximately 56 kDa. The recombinant protein consists of 495 amino acids and possesses six asparagine‑linked glycosylation sites, four of which carry a bis‑mannose-6–phosphate residue for specific cellular recognition. Post-translational modification of Cys53 produces the catalytic amino acid residue, Cα-formylglycine, which is required for enzyme activity. NAGLAZYME has a specific activity of approximately 70 units per mg of protein content. One activity unit is defined as the amount of enzyme required to convert 1 micromole of 4-methylumbelliferyl sulfate to 4-methylumbelliferone and free sulfate per minute at 37°C.

NAGLAZYME is intended for intravenous infusion and is supplied as a sterile, nonpyrogenic, colorless to pale yellow, clear to slightly opalescent solution that must be diluted with 0.9% Sodium Chloride Injection, USP, prior to administration. NAGLAZYME is supplied in clear Type I glass 5 mL vials. Each vial provides 5 mg galsulfase, 43.8 mg sodium chloride, 6.20 mg sodium phosphate monobasic monohydrate, 1.34 mg sodium phosphate dibasic heptahydrate, and 0.25 mg polysorbate 80 in a 5 mL extractable solution with pH of approximately 5.8. NAGLAZYME does not contain preservatives. Each vial is for single use only.

12 CLINICAL PHARMACOLOGY

12.1 Mechanism of Action

Mucopolysaccharide storage disorders are caused by the deficiency of specific lysosomal enzymes required for the catabolism of GAG. MPS VI is characterized by the absence or marked reduction in N-acetylgalactosamine 4-sulfatase. The sulfatase activity deficiency results in the accumulation of the GAG substrate, dermatan sulfate, throughout the body. This accumulation leads to widespread cellular, tissue, and organ dysfunction. NAGLAZYME is intended to provide an exogenous enzyme that will be taken up into lysosomes and increase the catabolism of GAG. Galsulfase uptake by cells into lysosomes is most likely mediated by the binding of mannose-6-phosphate-terminated oligosaccharide chains of galsulfase to specific mannose-6-phosphate receptors.

12.2 Pharmacodynamics

The responsiveness of urinary GAG to dosage alterations of NAGLAZYME is unknown, and the relationship of urinary GAG to other measures of clinical response has not been established.

12.3 Pharmacokinetics

The pharmacokinetic parameters of galsulfase were evaluated in 13 patients with MPS VI who received 1 mg/kg of NAGLAZYME as a weekly 4-hour infusion for 24 weeks. The pharmacokinetic parameters at Week 1 and Week 24 are shown in Table 2. Galsulfase pharmacokinetic parameters listed in Table 2 require cautious interpretation because of large assay variability.

Table 2: Pharmacokinetic Parameters (Median, Range) of Galsulfase in Patients with MPS VI
Pharmacokinetic Parameter | Week 1 | Week 24
Cmax (mcg/mL) | 0.8 (0.4 to 1.3) | 1.5 (0.2 to 5.5)
AUC0-t (hr•mcg/mL) [Area under the plasma galsulfase concentration-time curve from start of infusion to 60 minutes post infusion] | 2.3 (1.0 to 3.5) | 4.3 (0.3 to 14.2)
Vz (mL/kg) | 103 (56 to 323) | 69 (59 to 2,799)
CL (mL/kg/min) | 7.2 (4.7 to 10.5) | 3.7 (1.1 to 55.9)
Half-life (min) | 9 (6 to 21) | 26 (8 to 40)

12.6 Immunogenicity

The observed incidence of anti-drug antibodies (ADA) is highly dependent on the sensitivity and specificity of the assay. Differences in assay methods preclude meaningful comparisons of the incidence of ADA in the studies described below with the incidence of ADA in other studies, including those of NAGLAZYME or of other galsulfase products.

In four clinical studies [see Clinical Studies (14)] of MPS VI patients 5 to 29 years of age, 53 of 54 (98%) NAGLAZYME-treated patients developed anti-galsulfase IgG antibodies (referred to as ADA) within 4 to 8 weeks of treatment.

In the placebo-controlled study, 19 of 19 (100%) NAGLAZYME-treated patients developed ADA. Neutralizing antibodies were detected in 4 of 16 (25%) patients who had samples available for neutralizing antibody assessments.

There was no identified clinically significant effect of ADA on infusion-associated reactions, urinary glycosaminoglycan (GAG) levels, or endurance measures. There is insufficient information to characterize the effects of ADA on pharmacokinetics of galsulfase.

13 NONCLINICAL TOXICOLOGY

13.1 Carcinogenesis, Mutagenesis, Impairment of Fertility

Long-term studies in animals to evaluate carcinogenic potential or studies to evaluate mutagenic potential have not been performed with galsulfase.

Galsulfase at intravenous doses up to 3.0 mg/kg (about 0.5 times the recommended human dose of 1 mg/kg based on body surface area) was found to have no effect on the fertility and reproductive performance of male and female rats.

14 CLINICAL STUDIES

A total of 56 patients with MPS VI, ages 5 years to 29 years, were enrolled in four clinical studies. The majority of patients had severe manifestations of the disease as evidenced by poor performance on a test of physical endurance.

In the randomized, double-blind, multicenter, placebo-controlled clinical trial, 38 patients with MPS VI received 1 mg/kg NAGLAZYME or placebo, once-weekly for 24 weeks. The patients’ ages ranged from 5 to 29 years. Enrollment was restricted to patients with a 12‑minute walk distance of 5 to 400 meters. All patients were treated with antihistamines prior to each infusion.

The NAGLAZYME-treated group showed greater mean increases in the distance walked in 12 minutes (12‑minute walk test, 12‑MWT) and in the rate of stair climbing in a 3-minute stair climb test, compared with the placebo group (Table 3).

Table 3: Results from Placebo-Controlled Clinical Study
 | NAGLAZYME |  |  | Placebo |  |  | NAGLAZYME vs. Placebo
 | Baseline | Week 24 | Change | Baseline | Week 24 | Change | Difference in Changes
N | 19 | 19 | 19 | 20 | 19 [One patient in the placebo group dropped out after 4 weeks of infusion] | 19
Results from the 12-Minute Walk Test (Meters)
Mean ± SD Median Percentiles (25th, 75th) | 227 ± 170 210 90, 330 | 336 ± 227 316 125, 483 | 109 ± 154 48 7, 183 | 381 ± 202 365 256, 560 | 399 ± 217 373 204, 573 | 26 ± 122 34 –3, 89 | 83 ± 45 [Observed mean of NAGLAZYME - Placebo ± SE] 92 ± 40 [Model-based mean of NAGLAZYME - Placebo ± SE, adjusted for baseline] (p = 0.025), [p-value based on the model-based mean difference]
Results from 3-Minute Stair Climb Test (Stairs/Minute)
Mean ± SD Median Percentiles (25th, 75th) | 19.4 ± 12.9 16.7 10.0, 26.3 | 26.9 ± 16.8 22.8 14.8, 33.0 | 7.4 ± 9.9 5.2 2.2, 9.9 | 31.0 ± 18.1 24.7 18.1, 51.5 | 32.6 ± 19.6 29.0 14.2, 57.9 | 2.7 ± 6.9 4.3 1.0, 6.2 | 4.7 ± 2.8 5.7 ± 2.9 (p = 0.053),

Following the 24-week placebo-controlled study period, 38 patients received open-label NAGLAZYME for 72 weeks. Among the 19 patients who were initially randomized to NAGLAZYME and who continued to receive treatment for 72 weeks (total of 96 weeks), increases in the 12-MWT distance and in the rate of stair climbing were observed compared to the start of the open-label period (mean [ ± SD] change): 72 ± 116 meters and 5.6 ± 10.6 stairs/minute, respectively). Among the 19 patients who were randomized initially to placebo for 24 weeks, and then crossed over to treatment with NAGLAZYME, the increases after 72 weeks of NAGLAZYME treatment compared to the start of the open-label period, (mean [ ± SD] change): were 118 ± 127 meters and 11.1 ± 10.0 stairs/minute, for the 12-MWT and the rate of stair climbing, respectively.

Bioactivity was evaluated with urinary GAG concentration. Overall, 95% of patients showed at least a 50% reduction in urinary GAG levels after 72 weeks of treatment with NAGLAZYME. No patient receiving NAGLAZYME reached the normal range for urinary GAG levels [see Clinical Pharmacology (12.2)].

In an additional open-label extension study, patients receiving NAGLAZYME showed maintenance of initial improvement in endurance for approximately 240 weeks.

16 HOW SUPPLIED/STORAGE AND HANDLING

NAGLAZYME injection is supplied as a sterile colorless to pale yellow, clear to slightly opalescent solution in clear Type I glass 5 mL vials, containing 5 mg galsulfase (expressed as protein content) per 5 mL solution. The closure consists of a siliconized chlorobutyl rubber stopper and an aluminum seal with a plastic flip-off cap.

NDC 68135-020-01, 5 mL vial

Store NAGLAZYME under refrigeration at 2°C to 8°C (36°F to 46°F). Do not freeze or shake. Protect from light. This product contains no preservatives.

17 PATIENT COUNSELING INFORMATION

Hypersensitivity Reactions Including Anaphylaxis and Infusion Reactions

Advise the patient or caregiver that life-threatening hypersensitivity reactions, including anaphylaxis and infusion reactions, may occur with NAGLAZYME treatment.

Advise the patient or caregiver that anaphylaxis has occurred during the early course of enzyme replacement therapy and after extended duration of therapy.

Inform the patient or caregiver of the symptoms of life-threatening hypersensitivity reactions, including anaphylaxis, and infusion reactions and to seek immediate medical care should symptoms occur [see Warnings and Precautions (5.1, 5.5)].

Respiratory Adverse Reactions

Advise the patient or caregiver to report immediately to a healthcare provider if signs or symptoms of cardiac or respiratory decompensation occur during or following an infusion [see Warnings and Precautions (5.3, 5.4)]. Inform patients using supplemental oxygen or continuous positive airway pressure (CPAP) during sleep to have these treatments readily available during infusion or extreme drowsiness/sleep induced by antihistamine use.

NAGLAZYME is manufactured and distributed by:
BioMarin Pharmaceutical Inc.
Novato, CA 94949
US License Number 1649
1-866-906-6100 (phone)

NAGLAZYME® is a registered trademark of BioMarin.

Packaging Components

NDC 68135-020-01

Naglazyme®
(GALSULFASE)

5 mg/5 mL
(1 mg/mL)

Concentrated Solution For Intravenous Infusion Only

Must be diluted prior to use.

Rx Only

Naglazyme Carton